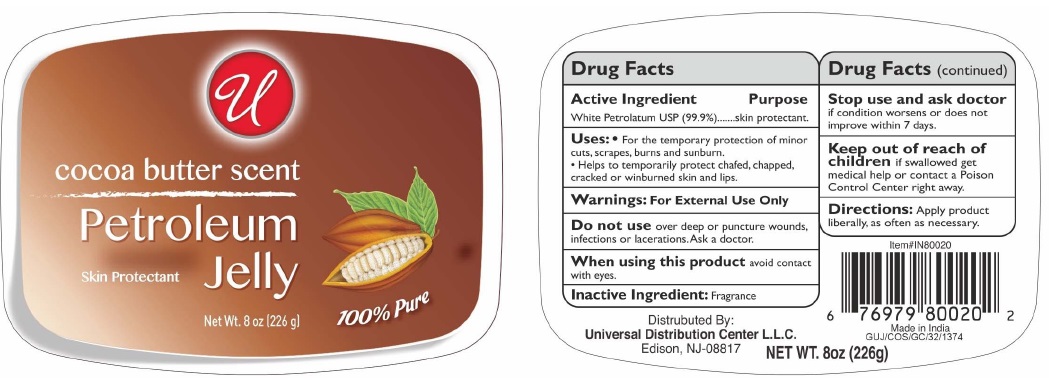 DRUG LABEL: UNIVERSAL COCOA BUTTER SCENT PETROLEUM
NDC: 52000-119 | Form: JELLY
Manufacturer: Universal Distribution Center LLC
Category: otc | Type: HUMAN OTC DRUG LABEL
Date: 20241204

ACTIVE INGREDIENTS: PETROLATUM 99.9 g/100 g
INACTIVE INGREDIENTS: WATER

UNIVERSAL COCOA BUTTER SCENT PETROLEUM

Active ingredient

White Petrolatum USP (99.9 %)

Purpose

Skin Protectant

Uses

- For the temporary protection of minor cuts, scrapes, burns and sunburn.
- Helps to temporarily protect chafed, chapped, cracked or windburned skin and lips.

Warnings

For External Use Only.

Do not use over deep or puncture wounds, infections or lacerations. Ask a doctor.

When using this product avoid contact with eyes.

Stop use and ask doctor if condition worsens or does not improve within 7 days.

Keep out of reach of children if swallowed get medical help or contact a Poison Control Center right away.

Directions

Apply product as liberally, as often as necessary.

Inactive ingredients

Fragrance

PRINCIPAL DISPLAY PANEL

Universal Cocoa Butter Scent Petroleum
Jelly
Net Wt. 8 OZ (226 g)